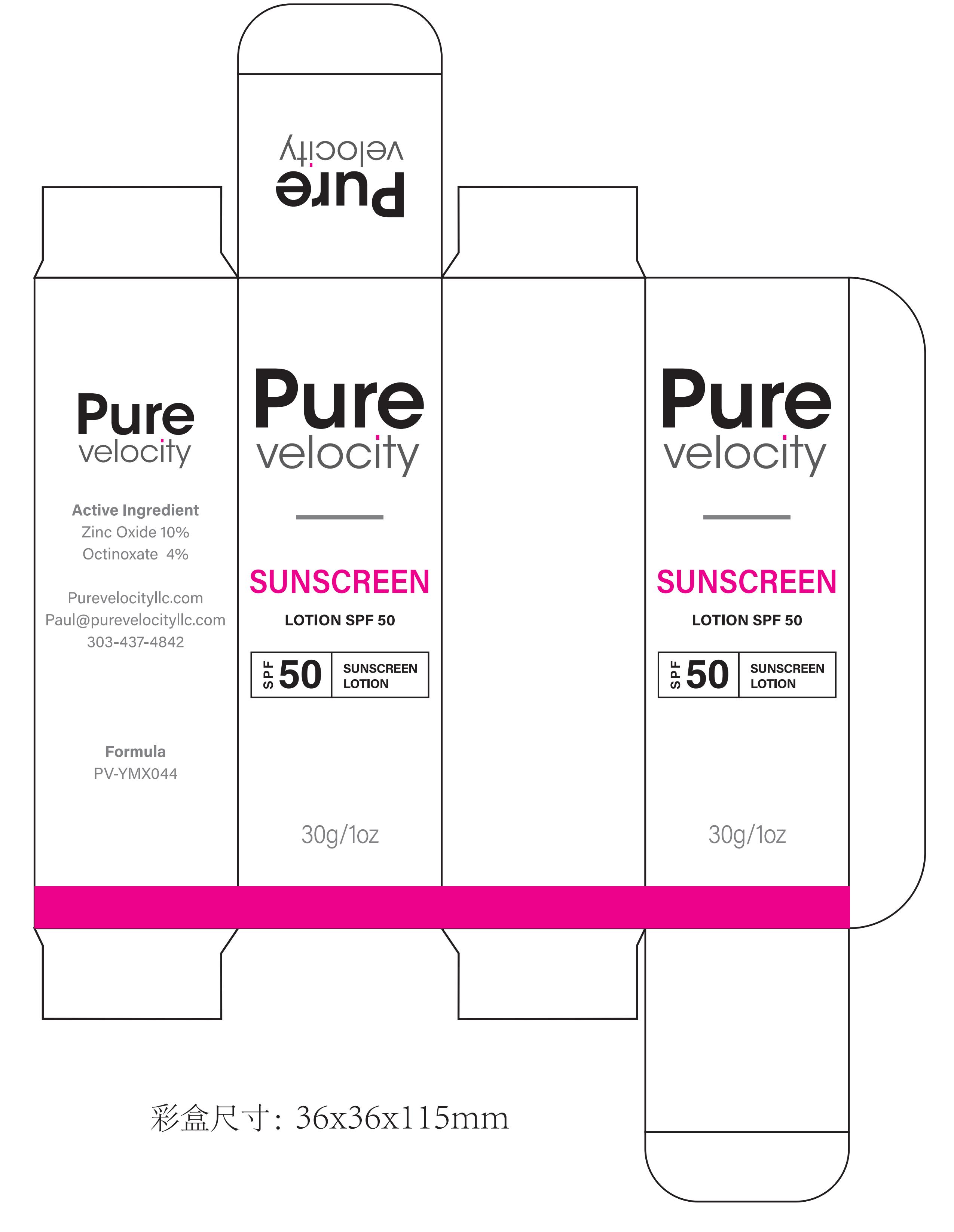 DRUG LABEL: Pure velocity SUNSCREEN  SPF 50
NDC: 60771-0031 | Form: LIQUID
Manufacturer: Guangzhou Haishi Biological Technology Co., Ltd.
Category: otc | Type: HUMAN OTC DRUG LABEL
Date: 20250930

ACTIVE INGREDIENTS: ETHYLHEXYL METHOXYCINNAMATE 1.5 g/100 g; ZINC OXIDE 3 g/100 g
INACTIVE INGREDIENTS: PETROLATUM; HYDROXYETHYL ACRYLATE/SODIUM ACRYLOYLDIMETHYL TAURATE COPOLYMER (45000 MPA.S AT 1%); PEG-7 TRIMETHYLOLPROPANE COCONUT ETHER; ISOPROPYL PALMITATE; POLYETHER-1 (2800 MPA.S); .ALPHA.-BUTYLDIMETHYLSILYL-AND .OMEGA.-3-METHACRYLOXYPROPYLDIMETHYLSILYL-TERMINATED POLYDIMETHYLSILOXANE (10000 MW); CITRIC ACID; WATER; POLYISOBUTYLENE (1000 MW); SODIUM HYALURONATE; 1,2-BUTANEDIOL; IODOPROPYNYL BUTYLCARBAMATE; CETEARYL GLUCOSIDE; .ALPHA.-TOCOPHEROL ACETATE; TRIETHOXYCAPRYLYLSILANE; PHENOXYETHANOL

Active Ingredients

ETHYLHEXYL METHOXYCINNAMATE

ZINC OXIDE

Purpose

SUNSCREEN

Uses

If used as directed with other sun protection measures(see Directions)，
decreases the risk of skin cancer and early skin aging caused by the sun.

Warnings

For external use only

Stop Use

Rinse with wate to remove.
Stop use and ask doctor if rash occurs.

Do not use on damaged or broken skin.

When Using

When using this product keep out of eyes.

Keep Out Of Reach Of Children

Dosage & administration

Squeeze out an appropriate amount of Sunscreen and spread evenly on skin.

Inactive ingredients

WATER

PETROLATUM

ISOPROPYL PALMITATE

CETEARYL GLUCOSIDE

POLYDIMETHYLSILOXANE

HYDROXYETHYL ACRYLATE/SODIUM ACRYLOYLDIMETHYL TAURATE COPOLYMER

POLYISOBUTYLENE

PEG-7 TRIMETHYLOLPROPANE COCONUT ETHER

SODIUM HYALURONATE

TOCOPHERYL ACETATE

POLYETHER-1

CITRIC ACID

OLEANOL POLYETHER-3 PHOSPHATE

PHENOXYETHANOL

BUTANEDIOL

IODOPROPYNYL BUTYLCARBAMATE

TRIETHOXYOCTYLSILANE